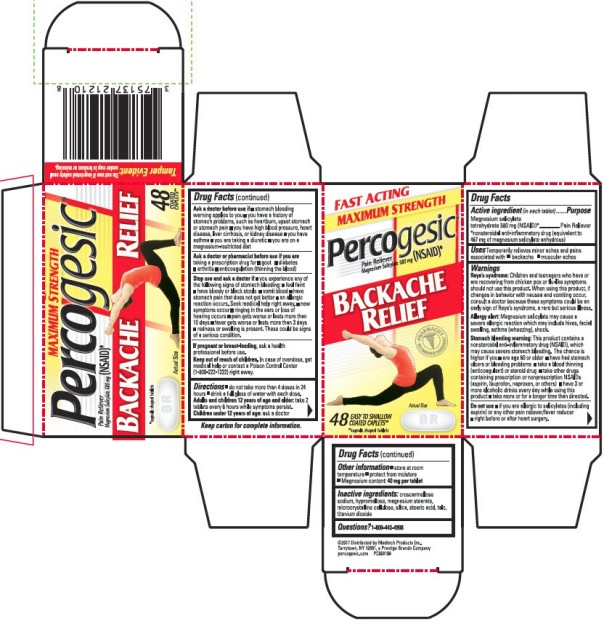 DRUG LABEL: Percogesic
NDC: 63029-051 | Form: TABLET, COATED
Manufacturer: Medtech Products Inc.
Category: otc | Type: HUMAN OTC DRUG LABEL
Date: 20241209

ACTIVE INGREDIENTS: MAGNESIUM SALICYLATE 467 mg/1 1
INACTIVE INGREDIENTS: CROSCARMELLOSE SODIUM; HYPROMELLOSE, UNSPECIFIED; MAGNESIUM STEARATE; MICROCRYSTALLINE CELLULOSE; SILICON DIOXIDE; STEARIC ACID; TALC; TITANIUM DIOXIDE

Percogesic 63029-051-48

PERCOGESIC- magnesium salicylate tablet, coated Medtech Products Inc.

Disclaimer: Most OTC drugs are not reviewed and approved by FDA, however they may be marketed if they comply with applicable regulations and policies. FDA has not evaluated whether this product complies.

Percogesic Maximum Strength Backache Relief

Drug Facts

Active ingredient (in each tablet)

Magnesium salicylate tetrahydrate 580 mg (NSAID)*

*nonsteroidal anti-inflammatory drug (equivalent to 467 mg of magnesium salicylate anhydrous)

Purpose

Pain reliever

Uses

Temporarily relieves minor aches and pains associated with

- backache
- muscular aches

Warnings

Reye’s syndrome: Children and teenagers who have or are recovering from chicken pox or flu-like symptoms should not use this product. When using this product, if changes in behavior with nausea and vomiting occur, consult a doctor because these symptoms could be an early sign of Reye’s syndrome, a rare but serious illness.

Allergy alert: Magnesium salicylate may cause a severe allergic reaction which may include hives, facial swelling, asthma (wheezing), shock.

Stomach bleeding warning: This product contains a nonsteroidal anti-inflammatory drug (NSAID), which may cause severe stomach bleeding. The chance is higher if you ■ are age 60 or older ■ have had stomach ulcers or bleeding problems ■ take a blood thinning (anticoagulant) or steroid drug ■ take other drugs containing prescription or nonprescription NSAIDs (aspirin, ibuprofen, naproxen, or others) ■ have 3 or more alcoholic drinks every day while using this product ■ take more or for a longer time than directed.

Do not use

- if you are allergic to salicylates (including aspirin) or any other pain reliever/fever reducer
- right before or after heart surgery

Ask a doctor before use if

- stomach bleeding warning applies to you
- you have a history of stomach problems, such as heartburn, upset stomach or stomach pain
- you have high blood pressure, heart disease, liver cirrhosis, or kidney disease
- you have asthma
- you are taking a diuretic
- you are on a magnesium-restricted diet

Ask a doctor or pharmacist before use if you are

taking a prescription drug for

- gout
- diabetes
- arthritis
- anticoagulation (thinning the blood)

Stop use and ask a doctor if

you experience any of the following signs of stomach bleeding:

- feel faint
- have bloody or black stools
- vomit blood
- have stomach pain that does not get better
- an allergic reaction occurs. Seek medical help right away.
- new symptoms occur
- ringing in the ears or loss of hearing occurs
- pain gets worse or lasts more than 10 days
- fever gets worse or lasts more than 3 days
- redness or swelling is present. These could be signs of a serious condition.

If pregnant or breast-feeding

ask a health professional before use.

Keep out of reach of children.

In case of overdose, get medical help or contact a Poison Control Center (1-800-222-1222) right away.

Directions

do not take more than 4 doses in 24 hours. Drink a full glass of water with each dose.

Adults and children 12 years of age and older: take 2 tablets every 6 hours while symptoms persist.

Children under 12 years of age: ask a doctor

Other information

- store at room temperature
- protect from moisture
- Magnesium content: 40 mg per tablet

Inactive ingredients

croscarmellose sodium, hypromellose, magnesium stearate, microcrystalline cellulose, silica, stearic acid, talc, titanium dioxide

Questions?

1-800-443-4908

PRINCIPAL DISPLAY PANEL

PERCOGIS MAXIMUM STRENGTH BACKACHE RELIEF 48 COATED CAPLETS